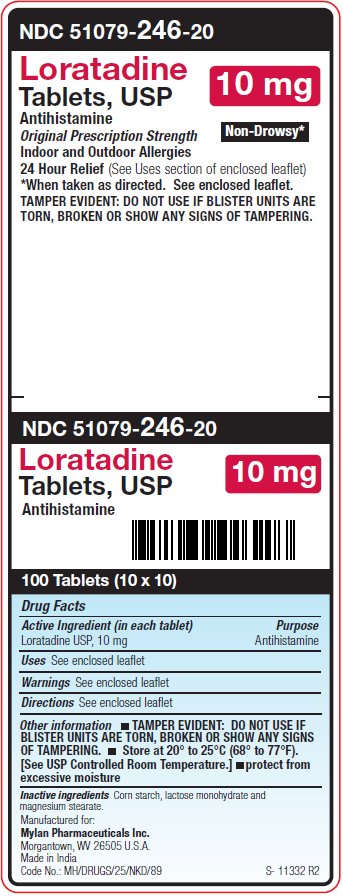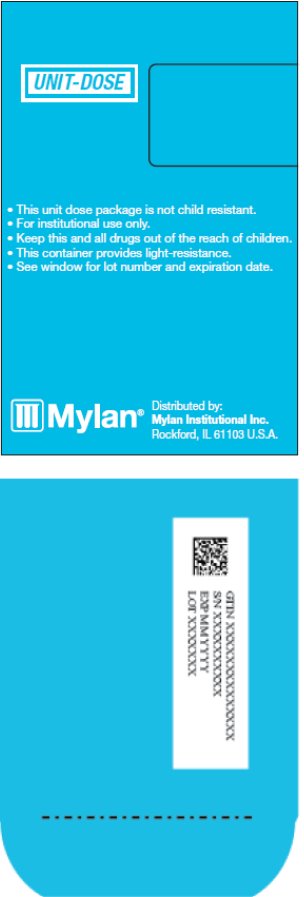 DRUG LABEL: Loratadine
NDC: 51079-246 | Form: TABLET
Manufacturer: Mylan Institutional Inc.
Category: otc | Type: HUMAN OTC DRUG LABEL
Date: 20250722

ACTIVE INGREDIENTS: LORATADINE 10 mg/1 1
INACTIVE INGREDIENTS: STARCH, CORN; LACTOSE MONOHYDRATE; MAGNESIUM STEARATE

Drug Facts

Original Prescription Strength Non-Drowsy*

Indoor and Outdoor Allergies

*When taken as directed. See Drug Facts Panel.

TAMPER EVIDENT: DO NOT USE IF BLISTER UNITS ARE TORN, BROKEN OR SHOW ANY SIGNS OF TAMPERING.

Active Ingredient (in each tablet)

Loratadine USP, 10 mg

Purpose

Antihistamine

Uses

temporarily relieves these symptoms due to hay fever or other upper respiratory allergies:

- runny nose
- itchy, watery eyes
- sneezing
- itching of the nose or throat

Warnings

Do not use

if you have ever had an allergic reaction to this product or any of its ingredients.

Ask a doctor before use if you have

liver or kidney disease. Your doctor should determine if you need a different dose.

When using this product

do not take more than directed. Taking more than directed may cause drowsiness.

Stop use and ask a doctor if

an allergic reaction to this product occurs. Seek medical help right away.

If pregnant or breast-feeding,

ask a health professional before use

Keep out of reach of children

In case of overdose, get medical help or contact a Poison Control Center right away.

Directions (24 Hour Relief)

adults and children 6 years and over | 1 tablet daily; not more than 1 tablet in 24 hours
children under 6 years of age | ask a doctor
consumers with liver or kidney disease | ask a doctor

Other information

- TAMPER EVIDENT: DO NOT USE IF BLISTER UNITS ARE TORN, BROKEN OR SHOW ANY SIGNS OF TAMPERING.
- Store at 20° to 25°C (68° to 77°F). [See USP Controlled Room Temperature.]
- protect from excessive moisture

Inactive Ingredients

Corn starch, lactose monohydrate and magnesium stearate.

Questions or comments?

1-800-848-0462

- Serious side effects associated with use of this product may be reported to this number.

Manufactured for:
Mylan Pharmaceuticals Inc.
Morgantown, WV 26505 U.S.A.

Made in India

Code No.: MH/DRUGS/25/NKD/89

Distributed by:
Mylan Institutional Inc.
Rockford, IL 61103 U.S.A.

S-11333 R3
1/21

PACKAGE LABEL

PRINCIPAL DISPLAY PANEL – 10 mg

NDC 51079-246-20

Loratadine
Tablets, USP
10 mg

Antihistamine

Original Prescription Strength Non-Drowsy*

Indoor and Outdoor Allergies

24 Hour Relief(See Uses section of enclosed leaflet)

*When taken as directed. See enclosed leaflet.

TAMPER EVIDENT: DO NOT USE IF BLISTER UNITS ARE
TORN, BROKEN OR SHOW ANY SIGNS OF TAMPERING.